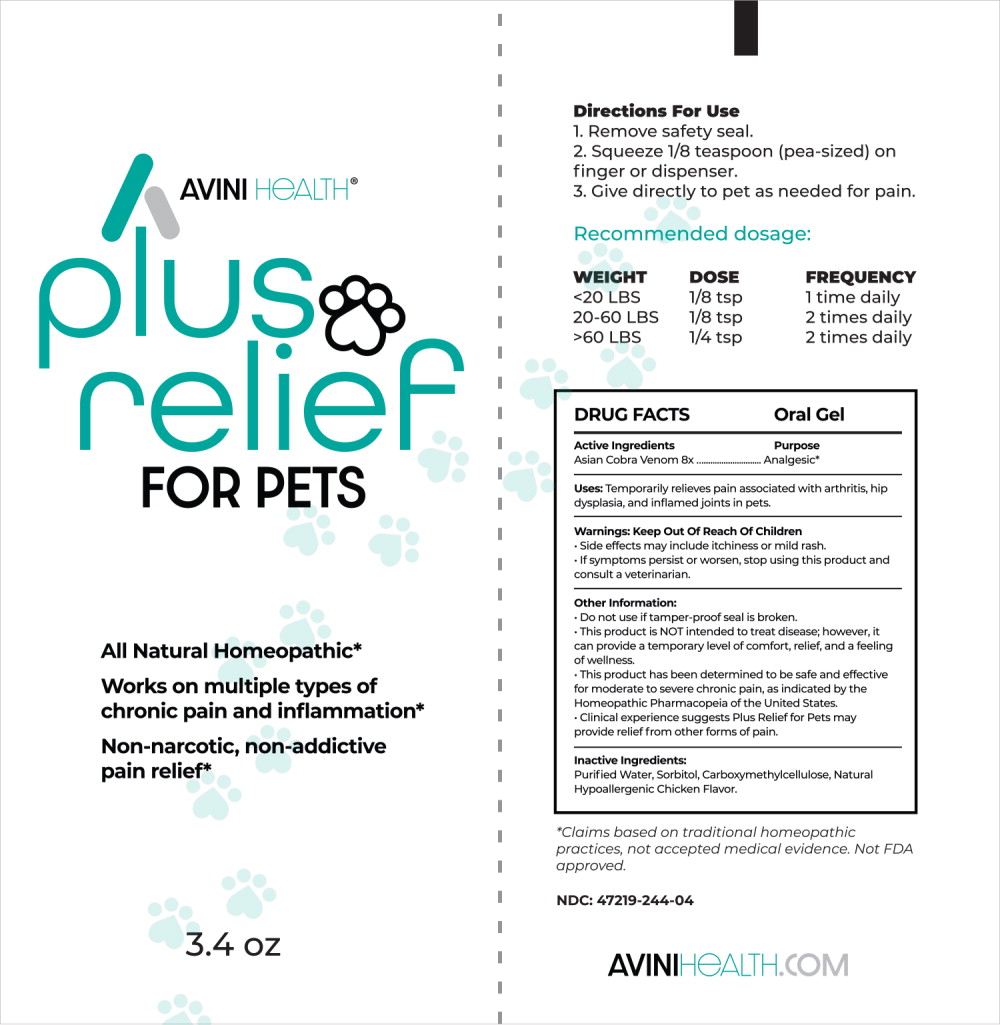 DRUG LABEL: Plus Relief For Pets
NDC: 47219-244 | Form: GEL
Manufacturer: Nutra Pharma Corporation
Category: homeopathic | Type: OTC ANIMAL DRUG LABEL
Date: 20251028

ACTIVE INGREDIENTS: NAJA NAJA VENOM 8 [hp_X]/1 mL
INACTIVE INGREDIENTS: WATER; SORBITOL; CARBOXYMETHYLCELLULOSE SODIUM, UNSPECIFIED

DRUG FACTS Oral Gel

Active Ingredients

Asian Cobra Venom 8x

Purpose

Analgesic*

*Claims based on traditional homeopathic practices, not accepted medical evidence. Not FDA approved.

Uses:

Temporarily relieves pain associated with arthritis, hip dysplasia, and inflamed joints in pets.

Warnings:

Keep Out Of Reach Of Children

- Side effects may include itchiness or mild rash.
- If symptoms persist or worsen, stop using this product and consult a veterinarian.

Other Information:

- Do not use if tamper-proof seal is broken.
- This product is NOT intended to treat disease; however, it can provide a temporary level of comfort, relief, and a feeling of wellness.
- This product has been determined to be safe and effective for moderate to severe chronic pain, as indicated by the Homeopathic Pharmacopeia of the United States.
- Clinical experience suggests Plus Relief for Pets may provide relief from other forms of pain.

Inactive Ingredients:

Purified Water, Sorbitol, Carboxymethylcellulose, Natural Hypoallergenic Chicken Flavor.

NDC: 47219-244-04

Directions For Use

1. Remove safety seal.
2. Squeeze 1/8 teaspoon (pea-sized) on finger or dispenser.
3. Give directly to pet as needed for pain.

Recommended dosage:

WEIGHT | DOSE | FREQUENCY
<20 LBS | 1/8 tsp | 1 time daily
20-60 LBS | 1/8 tsp | 2 times daily
>60 LBS | 1/4 tsp | 2 times daily

Principal Display Panel - 3.4 oz Tube Label

AVINI HEALTH®

pIus
relief
FOR PETS

All Natural Homeopathic*

Works on multiple types of chronic pain and inflammation*

Non-narcotic, non-addictive pain relief*

3.4 oz